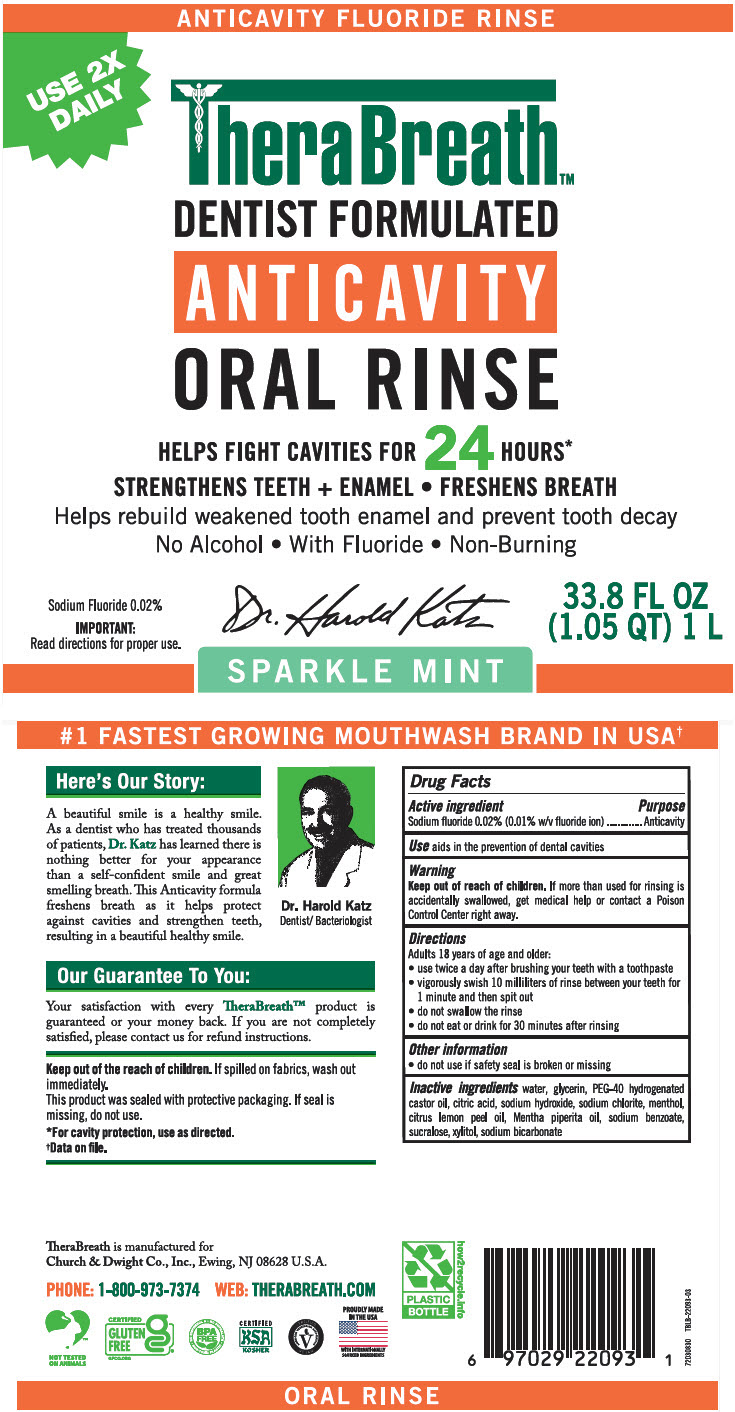 DRUG LABEL: TheraBreath Anticavity
NDC: 10237-265 | Form: RINSE
Manufacturer: Church & Dwight Co., Inc.
Category: otc | Type: HUMAN OTC DRUG LABEL
Date: 20250919

ACTIVE INGREDIENTS: SODIUM FLUORIDE 0.002 mg/10 mL
INACTIVE INGREDIENTS: WATER; GLYCERIN; POLYOXYL 40 HYDROGENATED CASTOR OIL; CITRIC ACID MONOHYDRATE; SODIUM HYDROXIDE; SODIUM CHLORITE; MENTHOL, UNSPECIFIED FORM; LEMON OIL, COLD PRESSED; PEPPERMINT OIL; SODIUM BENZOATE; SUCRALOSE; XYLITOL; SODIUM BICARBONATE

TheraBreath™Anticavity

Drug Facts

Active ingredient

Sodium fluoride 0.02% (0.01% w/v fluoride ion)

Purpose

Anticavity

Use

aids in the prevention of dental cavities

Warning

Keep out of reach of children. If more than used for rinsing is accidentally swallowed, get medical help or contact a Poison Control Center right away.

Directions

Adults 18 years of age and older:

- use twice a day after brushing your teeth with a toothpaste
- vigorously swish 10 milliliters of rinse between your teeth for 1 minute and then spit out
- do not swallow the rinse
- do not eat or drink for 30 minutes after rinsing

Other information

- do not use if safety seal is broken or missing

Inactive ingredients

water, glycerin, PEG-40 hydrogenated castor oil, citric acid, sodium hydroxide, sodium chlorite, menthol, citrus lemon peel oil, Mentha piperita oil, sodium benzoate, sucralose, xylitol, sodium bicarbonate

PRINCIPAL DISPLAY PANEL - 1 L Bottle Label

ANTICAVITY FLUORIDE RINSE

USE 2X
DAILY

TheraBreath™
DENTIST FORMULATED
ANTICAVITY
ORAL RINSE

HELPS FIGHT CAVITIES FOR 24 HOURS*
STRENGTHENS TEETH + ENAMEL • FRESHENS BREATH
Helps rebuild weakened tooth enamel and prevent tooth decay
No Alcohol • With Fluoride • Non-Burning

Sodium Fluoride 0.02%
IMPORTANT:
Read directions for proper use.

33.8 FL OZ
(1.05 QT) 1 L

SPARKLE MINT